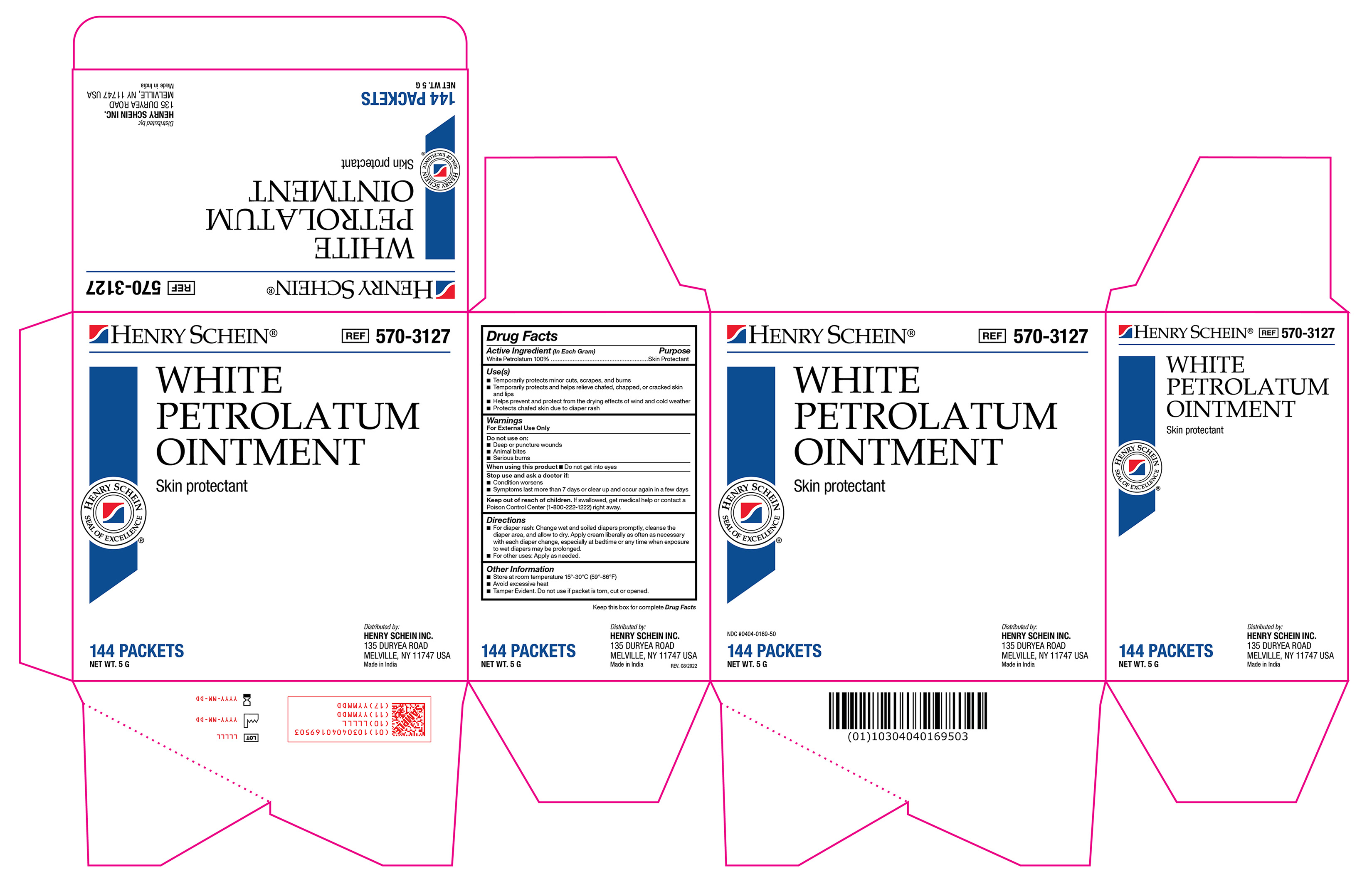 DRUG LABEL: White Petrolatum
NDC: 0404-0169 | Form: OINTMENT
Manufacturer: Henry Schein
Category: otc | Type: HUMAN OTC DRUG LABEL
Date: 20251125

ACTIVE INGREDIENTS: WHITE PETROLATUM 1 g/1 g

570-3127 Petrolatum Ointment NDC0404-0169-50

Active Ingredient

White Petrolatum 100%

Purpose

Skin Protectant

Use(s)

• Temporarily protects minor cuts, scrapes, and burns

• Temporarily protects and helps relieve chafed, chapped, or cracked skin and lips

• Helps prevent and protect from the drying effects of wind and cold weather

• Protects chafed skin due to diaper rash

Warnings

For External Use Only

Do not use on

• Deep or puncture wounds

• Animal bites

• Serious burns

When using this product

Avoid contact with eyes

Stop use and ask a doctor if

• Condition worsens

• Symptoms last more than 7 days or clear up and occur again within a few days

Keep out of reach of children.

If swallowed, get medical help or contact a Poison Control Center (1-800-222-1222) right away.

Directions

• For diaper rash: Change wet and soiled diapers promptly, cleanse the diaper area, and allow to dry. Apply liberally as often as necessary with each diaper change, especially at bedtime or anytime when exposure to wet diapers may be prolonged.

• For other uses: Apply as needed.

Other Information

• Store at room temperature 15º-30ºC (59º-86ºF)

• Avoid excessive heat

• Tamper evident. Do not use if packet is torn, cut, or opened.

Label

570-3127 Petrolatum Ointment